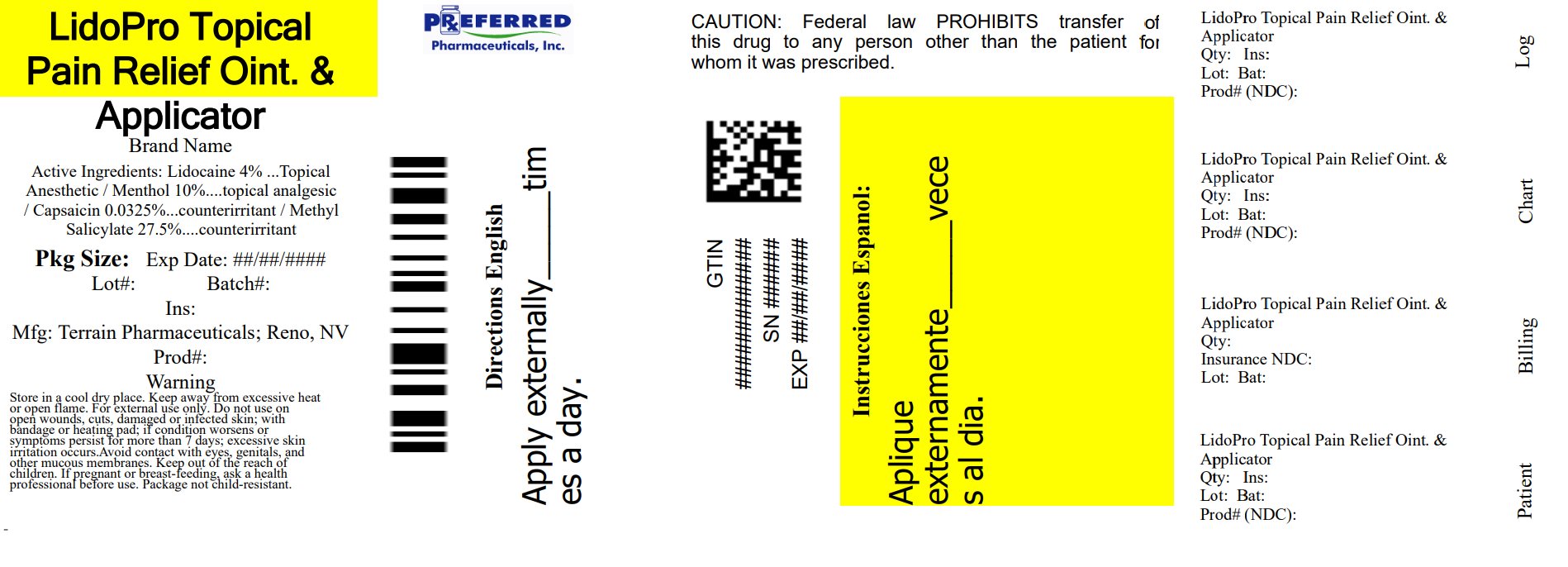 DRUG LABEL: LidoPro
NDC: 68788-8314 | Form: OINTMENT
Manufacturer: Preferred Pharmaceuticals Inc.
Category: otc | Type: HUMAN OTC DRUG LABEL
Date: 20250717

ACTIVE INGREDIENTS: CAPSAICIN 0.000325 g/1 g; LIDOCAINE HYDROCHLORIDE 0.04 g/1 g; MENTHOL, UNSPECIFIED FORM 0.1 g/1 g; METHYL SALICYLATE 0.275 g/1 g
INACTIVE INGREDIENTS: INULIN; STEARIC ACID; ALLANTOIN; ALOE VERA LEAF; AMMONIUM ACRYLOYLDIMETHYLTAURATE/VP COPOLYMER; CETYL ALCOHOL; CHAMOMILE; DIMETHICONE, UNSPECIFIED; EDETATE DISODIUM; ETHYLHEXYLGLYCERIN; GLYCERIN; GLYCERYL MONOSTEARATE; PEG-100 MONOSTEARATE; TROLAMINE; WATER; PHENOXYETHANOL

LidoPro 4% Ointment

Active Ingredient

Capsaicin 0.0325%

Purpose

Counterirritant

Active Ingredient

Lidocaine HCL 4%

Purpose

Topical Anesthetic

Active Ingredient

Menthol 10%

Purpose

Topical Analgesic

Active Ingredient

Methyl Salicylate 27.5%

Purpose

Counterirritant

Uses

For the temporary relief of joint pain and muscle pain associated with:

- Arthritis
- Simple Backache
- Muscle Sprains
- Muscle Strains

Warnings

For External Use Only

Do Not Use

- On damaged, irritated, or infected skin
- With a bandage or heating pad
- If you are allergic to any ingredients in this product

When Using This Product:

Avoid contact with eyes and mucus membranes

Stop Use and Ask a Doctor If:

- Conditions worsens
- Excessive skin irritation develops
- Symptoms persist for more than 7 days, or symptoms clear up and occur again within 3 days

If Pregnant orBreast-Feeding:

Ask a health professional before use.

Keep Out of Reach of Children:

If ingested seek medical help or contact a Poison Control Center immediately

Flammable:

Keep away from excessive heat or open flame

Directions

Adults and Children 12 Years of Age and Older:

- Clean and dry the affected area
- Apply product directly to your skin, up to 4 times daily affected area
- Wash hands immediately after use

Children Under 12 Years of Age: Consult physician

Other Information

- Store in a cool, dry place with lid tightly closed
- If the tamper-evident foil seal is not intact, do not use

Inactive Ingredients

Allantoin, Aloe Barbadensis Leaf Juice, Ammonium Acryloyldimethyltaurate/VP Copolymer, Cetyl Alcohol, Chamomilla Recutita Matricaria Flower Extract, Dimethicone, Disodium EDTA, Ethylhexylglycerin, Glycerin, Glyceryl Stearate, Inulin Lauryl Carbamate, PEG-100 Stearate, Phenoxyethanol, Stearic Acid, Triethanolamine, Water.

Questions or Comments?

info@terrainrx.com

Relabeled By: Preferred Pharmaceuticals Inc.

Principal Display Panel

NDC 53225-1020-1

Preferred Pharmaceuticals Inc. NDC 68788-8314-1